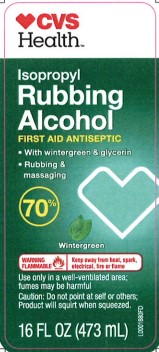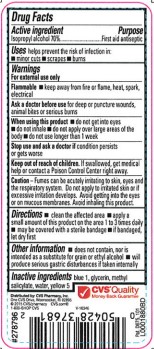 DRUG LABEL: Isopropyl Alcohol
NDC: 59779-845 | Form: LIQUID
Manufacturer: CVS Pharmacy, Inc.
Category: otc | Type: HUMAN OTC DRUG LABEL
Date: 20260203

ACTIVE INGREDIENTS: ISOPROPYL ALCOHOL 70 mL/100 mL
INACTIVE INGREDIENTS: FD&C BLUE NO. 1; GLYCERIN; METHYL SALICYLATE; WATER; FD&C YELLOW NO. 5

CVS 845.003/845AE
70% IPA with Wintergreen

Active ingredient

Isopropyl alcohol 70%

Purpose

First aid antiseptic

Uses

helps prevent the risk of infection in:

- minor cuts
- scrapes
- burns

Warnings

For external use only

Flammable. Keep away from fire or flame, heat, spark, electrical

Ask a doctor before use

if you have deep or puncture wounds, animal bites or serious burns

When using this product

- do not get into eyes
- do not inhale
- do not apply over large areas of the body
- do not use longer than 1 week

Stop use and ask a doctor if

condition persists or gets worse

Keep out of reach of children.

If swallowed, get medical help or contact a Poison Control Center right away.

Caution

Fumes can be acutely irritating to skin, eyes and the respiratory system. Do not apply to irritated skin or if excessive irritation develops. Avoid gettting into the eyes or on mucous membranes. Avoid inhaling this product.

Directions

- clean the affected area
- apply a small amount of this product on the area 1 to 3 times daily
- may be covered with a sterile bandage
- if bandaged, let dry first

Other information

- does not contain, nor is intended as a substitute for grain or ethyl alcohol
- will product serious gastric disturbances if taken internally

Inactive ingredients

blue 1, glycerin, methyl salicylate, water, yellow 5

ADVERSE REACTION

Distributed by: CVS Pharmacy, Inc.

One CVS Drive, Woonsocket, RI 02895

©2015 CVS/pharmacy cvs.com

1-800-SHOP CVS

Pat. D675,101

CVS Quality

Money Back Guarantee

Principal Panel Display

CVS HEALTH™

Isopropyl Rubbing Alcohol

FIRST AID ANTISEPTIC

- With wintergreen & glycerin
- Rubbing & massaging

70%

Wintergreen

WARNING FLAMMABLE - Keep away from heat, spark, electrical, fire or flame

Use only in a well-ventilated area; fumes may be harmful

Caution: Do not point at self or others; Product will squirt when squeezed

16 FL OZ (473 mL)